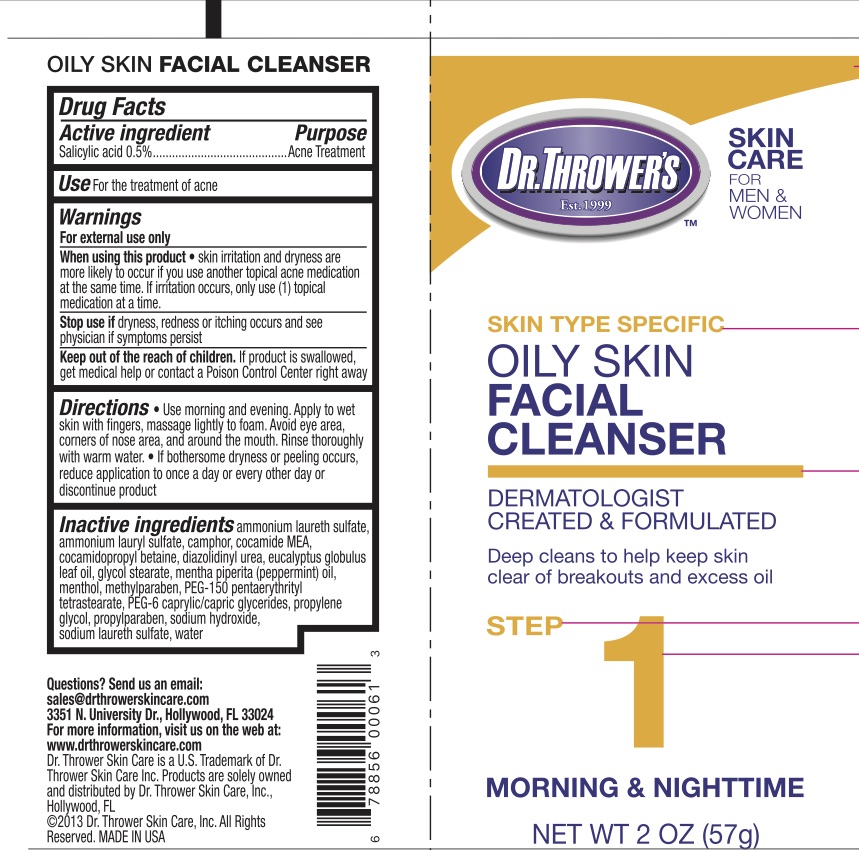 DRUG LABEL: Dr Throwers Oily Skin Facial Cleanser
NDC: 72839-613 | Form: LIQUID
Manufacturer: Derma Care Research Labs, LLC
Category: otc | Type: HUMAN OTC DRUG LABEL
Date: 20241220

ACTIVE INGREDIENTS: SALICYLIC ACID 2 g/100 g
INACTIVE INGREDIENTS: PEG-6 CAPRYLIC/CAPRIC GLYCERIDES; GLYCOL STEARATE; PEPPERMINT OIL; AMMONIUM LAURYL SULFATE; CAMPHOR (SYNTHETIC); COCO MONOETHANOLAMIDE; DIAZOLIDINYL UREA; EUCALYPTUS OIL; PEG-150 PENTAERYTHRITYL TETRASTEARATE; MENTHOL; POLYSORBATE 20; WATER; COCAMIDOPROPYL BETAINE; PROPYLENE GLYCOL; SODIUM HYDROXIDE; METHYLPARABEN; PROPYLPARABEN; SODIUM LAURETH SULFATE

Dr. Thrower's Oily Skin Facial Cleanser

Active Ingredient

Salicylic Acid 2%

Purpose

Acne treatment.

Uses

For the treatment of acne.

Warnings

For external use only.

When using this product skin irritation and dryness are more likely to occur if you use another topical acne medication at the same time. If irritation occurs, only use one topical acne medication at a time.

Stop use if dryness, redness, or itching occurs and see a physician if symptoms persist.

Keep Out of Reach of Children.

If swallowed, get medical help or contact a Poison Control Center right away.

Directions

Use morning and evening. Apply to wet skin with fingers, massage lightly to foam. Avoid eye area, corners of the nose are, and around the mouth. Rinse thoroughly with warm water. If bothersome dryness or peeling occurs, reduce application to once a day or every other day or discontinue the product.

Inactive Ingredients

Ammonium laureth sulfate, ammonium lauryl sulfate, camphor, cocamide MEA, cocamidopropyl betaine, diazolidinyl urea, eucalyptus globulus leaf oil, glycol stearate, mentha piperita (peppermint) oil, menthol, methylparaben, PEG-150 pentaerythrityl tetrastearate, PEG-6 caprylic/capric glycerides, propylene glycol, propylparaben, sodium hydroxide, sodium laureth sulfate, water.